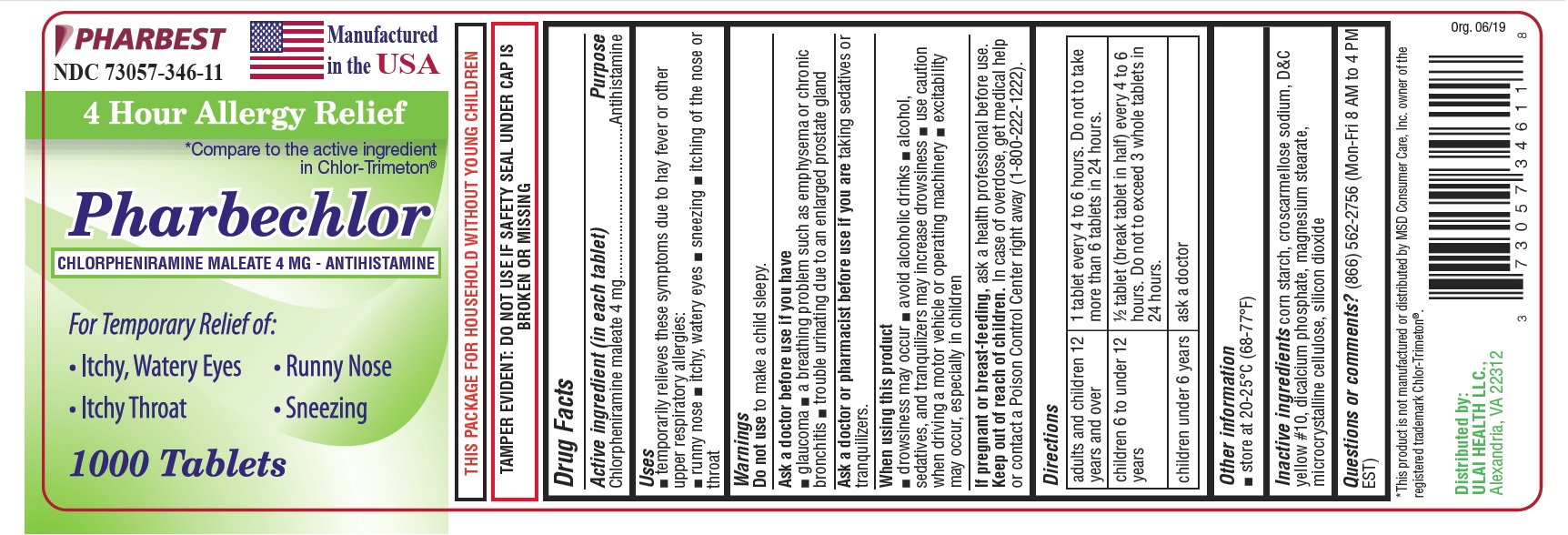 DRUG LABEL: Pharbechlor
NDC: 73057-346 | Form: TABLET
Manufacturer: Ulai Health LLC
Category: otc | Type: HUMAN OTC DRUG LABEL
Date: 20250120

ACTIVE INGREDIENTS: CHLORPHENIRAMINE MALEATE 4 mg/1 1
INACTIVE INGREDIENTS: CROSCARMELLOSE SODIUM; D&C YELLOW NO. 10; CALCIUM PHOSPHATE, DIBASIC, ANHYDROUS; MAGNESIUM STEARATE; CELLULOSE, MICROCRYSTALLINE; SILICON DIOXIDE; STARCH, CORN

Drug Facts

Active ingredient (in each tablet)

Chlorpheniramine maleate 4 mg

Purpose

Antihistamine

Uses

- temporarily relieves these following symptoms due to hay fever or other upper respiratory allergies:
- runny nose
- itchy, watery eyes
- sneezing
- itching of the nose or throat

Do not use

to make a child sleepy.

Ask a doctor before use if you have

- glaucoma
- a breathing problem such as emphysema or chronic bronchitis
- trouble urinating due to an enlarged prostate gland

Ask a doctor or pharmacist before use if you are

taking sedatives or tranquilizers.

When using this product

- drowsiness may occur
- avoid alcoholic drinks
- alcohol, sedatives, and tranquilizers may increase drowsiness
- use caution when driving a motor vehicle or operating machinery
- excitability may occur, especially in children

If pregnant or breast-feeding,

ask a health professional before use.

Keep out of reach of children.

In case of overdose, get medical help or contact a Poison Control Center right away (1-800-222-1222).

Directions

adults and children 12 years and over | 1 tablet every 4 to 6 hours. Do not take more than 6 tablets in 24 hours.
children 6 to under 12 years | 1/2 tablet (break tablet in half) every 4 to 6 hours. Do not to exceed 3 whole tablets in 24 hours.
children under 6 years | ask a doctor

Other information

- store at 20-25oC (68-77oF)

Inactive ingredients

corn starch, croscarmellose sodium, D&C yellow # 10, dicalcium phosphate, magnesium stearate, microcrystalline cellulose, silicon dioxide

Questions or comments?

(866) 562-2756 (Mon-Fri 8 AM to 4 PM EST)

PACKAGE LABEL

PHARBEST

NDC 73057-346-11

Manufactured in the USA

4 Hour Allergy Relief

*Compare to the active ingredient in Chlor-Trimeton®

Pharbechlor

CHLORPHENIRAMINE MALEATE 4 MG - ANTIHISTAMINE

For Temporary relief of:

•Itchy,Watery Eyes •Runny Nose

•Itchy Throat •Sneezing

1000 Tablets